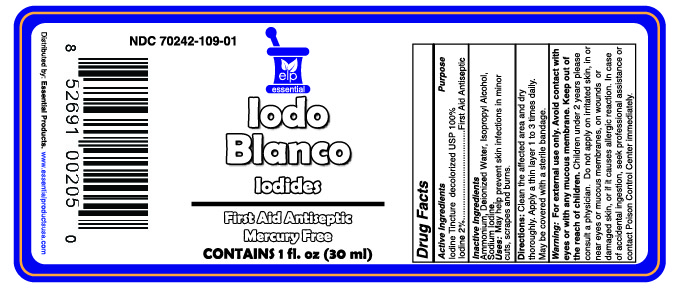 DRUG LABEL: Iodine Tincture White
NDC: 70242-109 | Form: SOLUTION/ DROPS
Manufacturer: Dannso Corp./d.b.a. Essential Products
Category: otc | Type: HUMAN OTC DRUG LABEL
Date: 20230101

ACTIVE INGREDIENTS: IODINE 20 mg/1 mL
INACTIVE INGREDIENTS: AMMONIUM SALICYLATE; Isopropyl Alcohol; Sodium Iodide; water

IODO BLANCO

Active ingredients

Iodine 2%

Purpose

First aid antiseptic

Use

First aid to help prevent sking infection in

- minor cuts
- scrapes
- burns

Warnings

For external use only. Avoid contact with eyes or with mucous membrane. Keep out of the reach of children. Children under 2 years please consult a physician. Do not apply on irritated skin, in or near eyes or mocuos memebranes, on wounds or damamged skin, or if it causes allergic reaction. In case of accidental ingestion, seek professional assistance or contact Poison Control Center immedialately.

Inactive Ingredient

Ammonium, Deionized Water, Isopropyl Alcohol, Sodium Iodine.

Stop use and ask a doctor

If condition persists or gets worse

Keep out of reach of children

If swallowed, get medical help or contact a Poison Control Center right away

Directions

- Clean the affected area and dry thorougkyapply.
- Apply a thin layer 1 to 3 times daily
- May be covered with a sterile bandage

Questions or Comments?

Distributed by

Essential Products Miami FL 33126

www.essentialproductsuse.com

Made in U.S.A.

Principal display panel

IODO BLANCO